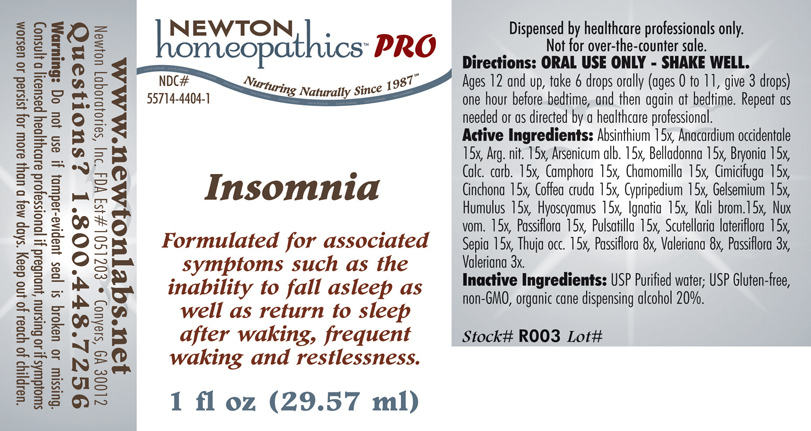 DRUG LABEL: Insomnia 
NDC: 55714-4404 | Form: LIQUID
Manufacturer: Newton Laboratories, Inc.
Category: homeopathic | Type: HUMAN PRESCRIPTION DRUG LABEL
Date: 20110601

ACTIVE INGREDIENTS: Wormwood 15 [hp_X]/1 mL; Anacardium Occidentale Fruit 15 [hp_X]/1 mL; Silver Nitrate 15 [hp_X]/1 mL; Arsenic Trioxide 15 [hp_X]/1 mL; Atropa Belladonna 15 [hp_X]/1 mL; Bryonia Alba Root 15 [hp_X]/1 mL; Oyster Shell Calcium Carbonate, Crude 15 [hp_X]/1 mL; Camphor (natural) 15 [hp_X]/1 mL; Matricaria Recutita 15 [hp_X]/1 mL; Black Cohosh 15 [hp_X]/1 mL; Cinchona Officinalis Bark 15 [hp_X]/1 mL; Arabica Coffee Bean 15 [hp_X]/1 mL; Cypripedium Parvifolum Root 15 [hp_X]/1 mL; Gelsemium Sempervirens Root 15 [hp_X]/1 mL; Hops 15 [hp_X]/1 mL; Hyoscyamus Niger 15 [hp_X]/1 mL; Strychnos Ignatii Seed 15 [hp_X]/1 mL; Potassium Bromide 15 [hp_X]/1 mL; Strychnos Nux-vomica Seed 15 [hp_X]/1 mL; Passiflora Incarnata Flowering Top 15 [hp_X]/1 mL; Pulsatilla Vulgaris 15 [hp_X]/1 mL; Scutellaria Lateriflora 15 [hp_X]/1 mL; Sepia Officinalis Juice 15 [hp_X]/1 mL; Thuja Occidentalis Leafy Twig 15 [hp_X]/1 mL; Passiflora Incarnata Flowering Top 8 [hp_X]/1 mL; Valerian 8 [hp_X]/1 mL; Passiflora Incarnata Flowering Top 3 [hp_X]/1 mL; Valerian 3 [hp_X]/1 mL

Insomnia

PRODUCT NAME & INDICATIONS SECTION

Insomnia Formulated for associated symptoms such as the inability to fall asleep as well as return to sleep after waking, frequent waking and restlessness.

DIRECTION SECTION

Directions: ORAL USE ONLY - SHAKE WELL. Ages 12 and up, take 6 drops orally (ages 0 to 11, give 3 drops) one hour before bedtime, and then again at bedtime. Repeat as needed or as directed by a healthcare professional.

ACTIVE INGREDIENT SECTION

Absinthium 15x, Anacardium occidentale 15x, Arg. nit. 15x, Arsenicum alb. 15x, Belladonna 15x, Bryonia 15x,Calc. carb. 15x, Camphora 15x, Chamomilla 15x, Cimicifuga 15x, Cinchona 15x, Coffea cruda 15x, Cypripedium 15x, Gelsemium 15x,Humulus 15x, Hyoscyamus 15x, Ignatia 15x, Kali brom.15x, Nux vom. 15x, Passiflora 15x, Pulsatilla 15x, Scutellaria lateriflora 15x,Sepia 15x, Thuja occ. 15x, Passiflora 8x, Valeriana 8x, Passiflora 3x,Valeriana 3x.

INACTIVE INGREDIENT SECTION

Inactive Ingredients: USP Purified Water; USP Gluten-free, non-GMO, organic cane dispensing alcohol 20%.

QUESTIONS? SECTION

www.newtonlabs.net Newton Laboratories, Inc. FDA Est # 1051203 - Conyers, GA 30012
Questions? 1.800.448.7256

WARNINGS SECTION

Warning: Do not use if tamper - evident seal is broken or missing. Consult a licensed healthcare professional if pregnant, nursing or if symptoms worsen or persist for more than a few days. Keep out of reach of children.

OTC - PREGNANCY OR BREAST FEEDING SECTION

Consult a licensed healthcare professional if pregnant, nursing or if symptoms worsen or persist for more than a few days.

OTC - KEEP OUT OF REACH OF CHILDREN SECTION

Keep out of reach of children